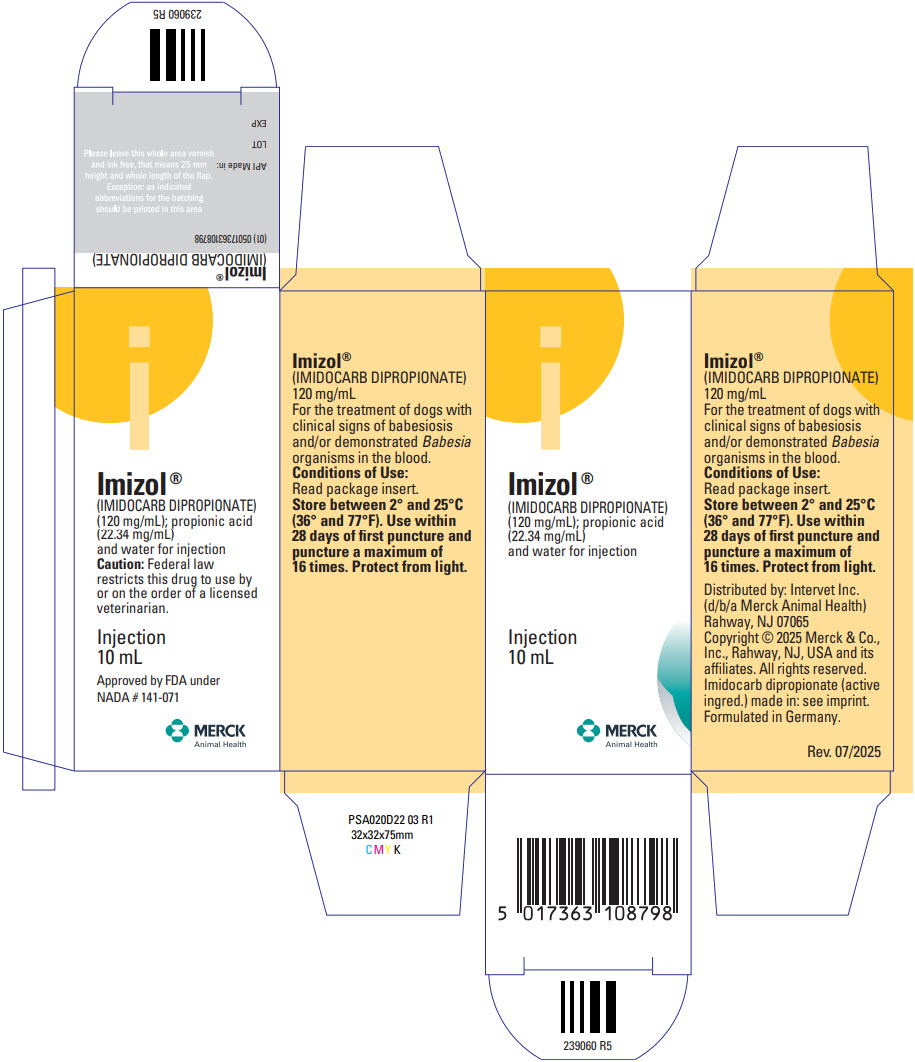 DRUG LABEL: Imizol
NDC: 0061-5158 | Form: INJECTION, SOLUTION
Manufacturer: Merck Sharp & Dohme Corp.
Category: animal | Type: PRESCRIPTION ANIMAL DRUG LABEL
Date: 20251125

ACTIVE INGREDIENTS: IMIDOCARB DIPROPIONATE 120 mg/1 mL

Imizol®
(IMIDOCARB DIPROPIONATE)

Approved by FDA under NADA # 141-071

Each mL contains 120 mg of imidocarb dipropionate.
Sterile solution for intramuscular or subcutaneous injection.

CAUTION: Federal law restricts this drug to use by or on the order of a licensed veterinarian.

DESCRIPTION:

IMIZOL (imidocarb dipropionate) is a sterile solution containing 120 mg/mL of imidocarb dipropionate suitable for intramuscular or subcutaneous administration. Imidocarb is chemically described as N,N'-bis[3-(4,5- dihydro-1H-imidazol-2-yl)-phenyl]urea dipropionate and has a molecular weight of 496.6. In addition to the active component, imidocarb dipropionate, the formulation also contains propionic acid (22.34 mg/mL), and water for injection.

INDICATIONS:

For the treatment of dogs with clinical signs of babesiosis and/or demonstrated Babesia organisms in the blood.

DOSAGE AND ADMINISTRATION:

Use intramuscularly or subcutaneously at a rate of 6.6 mg/kg (3mg/lb) body weight. Repeat the dose in two (2) weeks, for a total of two (2) treatments.

IMIZOL® DOSING GUIDE 6.6 mg/kg Body Weight
Animal Weight | IMIZOL Dosage | Animal Weight | IMIZOL Dosage
10 lb (4.5 kg) | 0.25 mL | 60 lb (27.3 kg) | 1.50 mL
20 lb (9.1 kg) | 0.50 mL | 80 lb (36.4 kg) | 2.00 mL
30 lb (13.6 kg) | 0.75 mL | 100 lb (45.5 kg) | 2.50 mL
40 lb (18.2 kg) | 1.00 mL

WARNINGS

WARNING: NOT FOR HUMAN USE. KEEP THIS AND ALL DRUGS OUT OF THE REACH OF CHILDREN. IN THE EVENT OF HUMAN EXPOSURE IMMEDIATELY CALL 303-595-4869, FOR MEDICAL ADVICE FOR HUMANS. Oncogenesis: Increased incidence of tumors was observed in rats given imidocarb.

PRECAUTION:

MUST NOT BE ADMINISTERED INTRAVENOUSLY. The safety and effectiveness of imidocarb have not been determined in puppies or in breeding, lactating, or pregnant animals. Risk versus benefit should be considered before using this drug in dogs with impaired lung, liver, or kidney function.

Do not use this product simultaneously with exposure to cholinesterase-inhibiting drugs, pesticides, or chemicals.

ADVERSE EFFECTS:

Adverse effects commonly seen are pain during injection and mild cholinergic signs such as salivation, nasal drip, or brief episodes of vomiting. Other effects seen less frequently are panting, restlessness, diarrhea, and mild injection site inflammation lasting one to several days. Rarely, injection site ulceration occurs, but the lesion is not resistant to healing.

If sever cholinergic signs occur, they may be reversed with atropine sulfate.

To report an adverse reaction, product-related problem, human exposure, or to obtain a copy of the Safety Data Sheet (SDS), please call Merck Animal Health Technical Services at 1-800-224-5318.

For additional information about adverse drug experience reporting for animal drugs, contact FDA at 1-888-FDAVETS or http://www.fda.gov/reportanimalae.

TOXICOLOGY:

IMIZOL solution was administered subcutaneously to four groups of 5 dogs at 2.2, 5.5, 7.7, or 9.9 mg/kg. The treatment was repeated 2 weeks later. There were no effects attributed to IMIZOL on body temperature, body weight, hematology, most clinical chemistries or gross pathology. At 9.9 mg/kg there was a slight increase in serum alanine aminotransferase (ALT, SGPT) and arginine aminotransferase (AST, SGOT) indicative of mild liver injury. Other effects noted were pain on injection, injection site swelling, and vomiting. Two of the injection sites ulcerated but healed readily without complication.

In a 90-day toxicity study, imidocarb was given orally to three groups of 8 dogs at the rate of 5, 20, or 80 mg/kg/day. The target organs of toxicity were liver and intestines. These results may have been influenced by the oral dosing route. In a pharmacokinetic study by Abdullah et al (1984)^1, imidocarb was administered to dogs intravenously at a dose of 4 mg/kg. One of 13 dogs died. The target organs of toxicity in this dog were lungs and kidneys, and some changes were noted in the liver and spleen.

The toxic syndrome involves lethargy, weakness, and anorexia, with possible signs of gastrointestinal, liver, kidney, and lung dysfunction.

PHARMACODYNAMICS:

The pharmacodynamics of imidocarb were studied in various species as described by Rao et al (1980)^2. The study suggests that there is a potential for adverse reactions mediated by the autonomic nervous system and especially through anticholinesterase mechanisms. Clinical experience in dogs at therapeutic dosages of less than 10 mg/kg body weight given intramuscularly or subcutaneously has established a pattern of adverse reactions. These reactions in descending order of frequency are: salivation, vomiting, and occasionally diarrhea.

HOW SUPPLIED

HOW SUPPLIED: IMIZOL® solution is packaged in 10 mL glass, sterile, multiple-dose vials.

STORAGE AND HANDLING

STORAGE: Store between 2° and 25°C (36° and 77°F). Use within 28 days of first puncture and puncture a maximum of 16 times. Protect from light.

REFERENCES:

^1A. S Abdullah et al, Veterinary Research Communications. 1984;(8):55-59.
^2K. S. Rao, Indian Veterinary Journal. 1980; 57(4):283-287

Copyright © 2025 Merck & Co., Inc., Rahway, NJ, USA and its affiliates. All rights reserved.
All rights reserved.
Formulated in Germany.

Rev. 07/2025

Distributed by: Intervet Inc. (d/b/a Merck Animal Health)
Rahway, NJ 07065

239059 R4

PRINCIPAL DISPLAY PANEL - 10 mL Vial Carton

Imizol®
(IMIDOCARB DIPROPIONATE)
(120 mg/mL); propionic acid
(22.34 mg/mL)
and water for injection

Injection
10 mL

MERCK
Animal Health